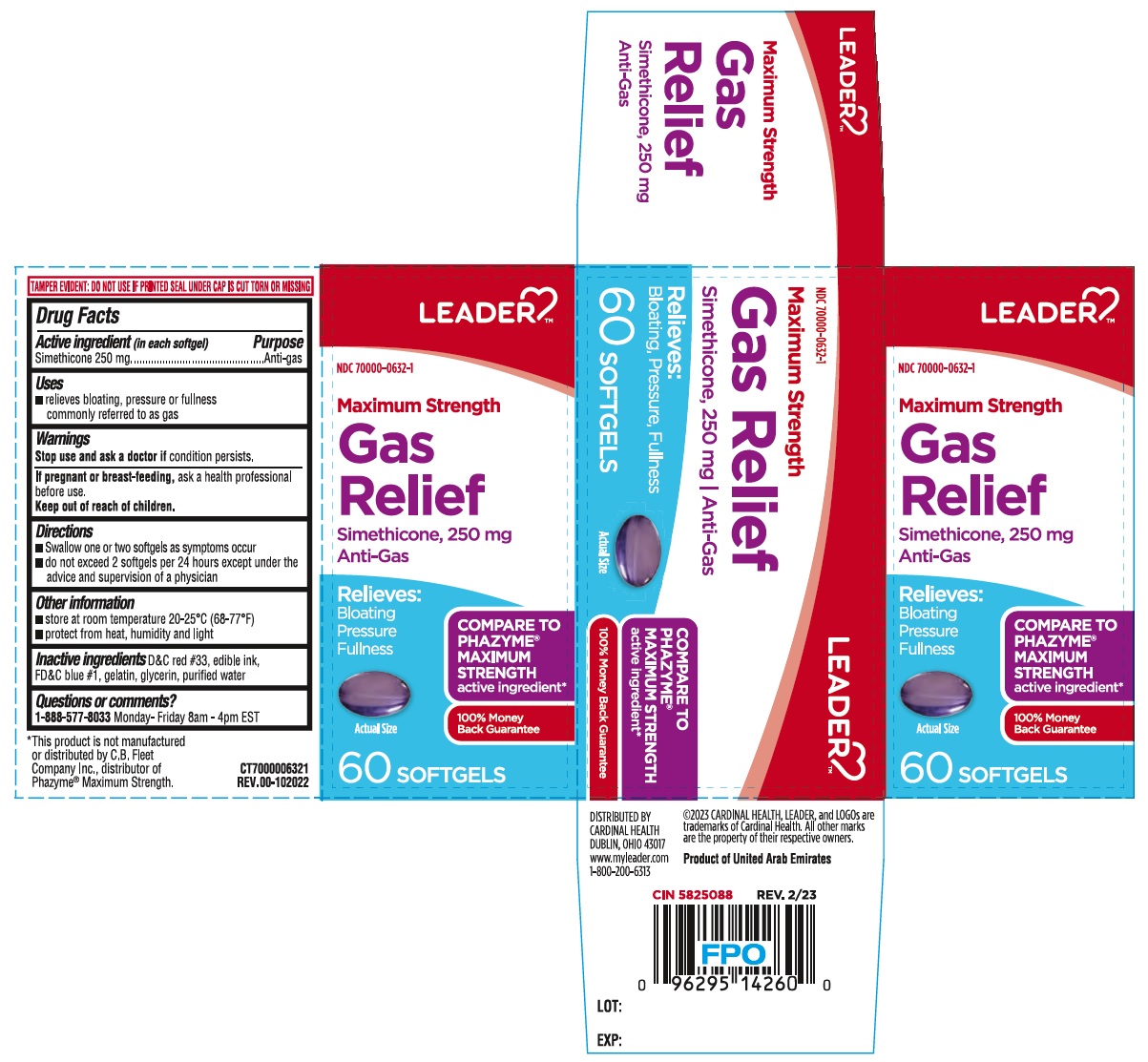 DRUG LABEL: Maximum Strength Gas Relief Softgel
NDC: 70000-0632 | Form: CAPSULE, LIQUID FILLED
Manufacturer: Cardinal Health 110, LLC. DBA Leader
Category: otc | Type: HUMAN OTC DRUG LABEL
Date: 20240111

ACTIVE INGREDIENTS: DIMETHICONE 250 mg/1 1
INACTIVE INGREDIENTS: D&C RED NO. 33; FD&C BLUE NO. 1; GELATIN, UNSPECIFIED; GLYCERIN; WATER

Maximum Strength Gas Relief Softgel

Active ingredient (in each softgel)

Simethicone 250 mg

Purpose

Anti-gas

Uses

• relieves bloating, pressure or fullness commonly referred to as gas

Warnings

Stop use and ask a doctor if condition persists.

If pregnant or breast-feeding, ask a health professional before use.

Keep out of reach of children.

Directions

• Swallow one or two softgels as symptoms occur
• do not exceed 2 softgels per 24 hours except under the advice and supervision of a physician

Other information

• store at room temperature 20-25°C (68-77°F)
• protect from heat, humidity and light

Inactive ingredients

D&C red #33, edible ink, FD&C blue #1, gelatin, glycerin, purified water

Questions or comments?

1-888-577-8033 Monday- Friday 8am - 4pm EST

LEADER™

Relieves:
Bloating
Pressure
Fullness

COMPARE TO PHAZYME® MAXIMUM STRENGTH active ingredient*

100% Money Back Guarantee

TAMPER EVIDENT: DO NOT USE IF PRINTED SEAL UNDER CAP IS CUT TORN OR MISSING

*This product is not manufactured or distributed by C.B. Fleet Company Inc., distributor of Phazyme® Maximum Strength.

DISTRIBUTED BY
CARDINAL HEALTH
DUBLIN, OHIO 43017
www.myleader.com
1-800-200-6313

©2023 CARDINAL HEALTH, LEADER, and LOGOs are trademarks of Cardinal Health. All other marks are the property of their respective owners.

Product of United Arab Emirates